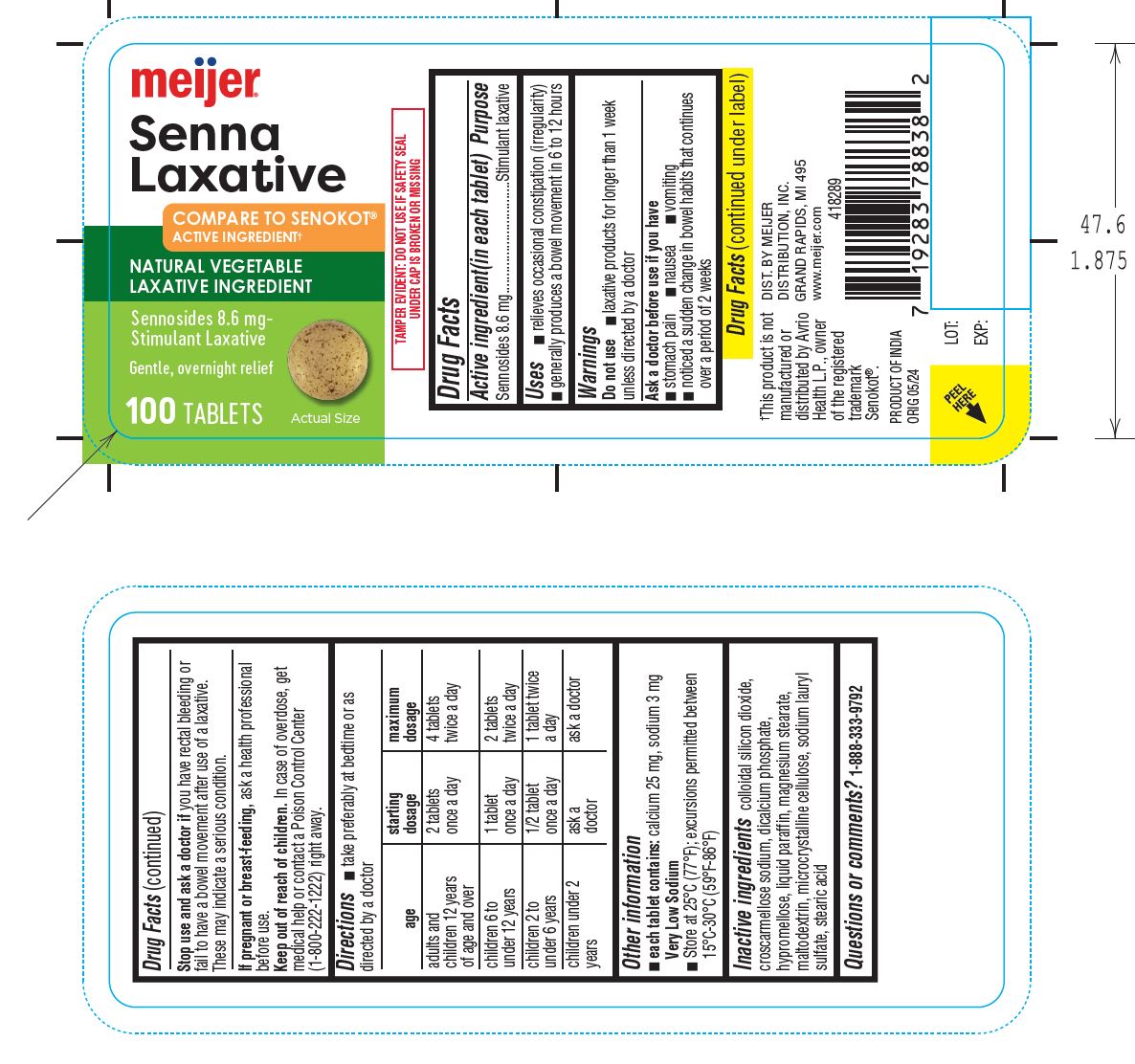 DRUG LABEL: Senna Laxative
NDC: 79481-0059 | Form: TABLET, FILM COATED
Manufacturer: Meijer, Inc.
Category: otc | Type: HUMAN OTC DRUG LABEL
Date: 20241220

ACTIVE INGREDIENTS: SENNOSIDES 8.6 mg/1 1
INACTIVE INGREDIENTS: SILICON DIOXIDE; CALCIUM PHOSPHATE, DIBASIC, ANHYDROUS; HYPROMELLOSE, UNSPECIFIED; MINERAL OIL; MAGNESIUM STEARATE; MALTODEXTRIN; MICROCRYSTALLINE CELLULOSE; SODIUM LAURYL SULFATE; STEARIC ACID

Senna Laxative Tablets